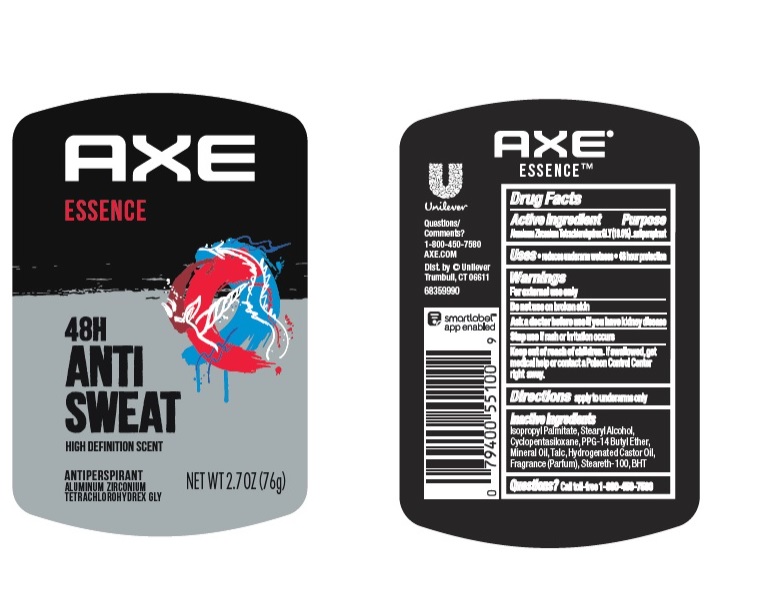 DRUG LABEL: Axe
NDC: 64942-1801 | Form: STICK
Manufacturer: Conopco Inc. d/b/a/ Unilever
Category: otc | Type: HUMAN OTC DRUG LABEL
Date: 20241110

ACTIVE INGREDIENTS: ALUMINUM ZIRCONIUM TETRACHLOROHYDREX GLY 19 g/100 g
INACTIVE INGREDIENTS: TALC; CYCLOMETHICONE 5; HYDROGENATED CASTOR OIL; BUTYLATED HYDROXYTOLUENE; STEARYL ALCOHOL; PPG-14 BUTYL ETHER; MINERAL OIL; STEARETH-100

Axe Essence 48H Anti Sweat Antiperspirant

AXE ESSENCE 48H ANTI SWEAT ANTIPERSPIRANT - aluminum zirconium tetrachlorohydrex gly stick

Axe Essence 48H Anti Sweat Antiperspirant

Drug Facts

Active ingredient

Aluminum Zirconium Tetrachlorohydrex GLY (19.0 %)

Purpose

antiperspirant

Uses

• reduces underarm wetness

• 48 Hour Protection

Warnings

• For externaluse only.
• Do not use on broken skin .
• Ask a doctor before use if you have kidney disease.
• Stop use if rash or irritation occurs.

• Keep out of reach of children.

If swallowed, get medical help or contact a Poison Control Center right away.

Directions

apply to underarms only

Inactive ingredients

Isopropyl Palmitate, Stearyl Alcohol, Cyclopentasiloxane, PPG-14 Butyl Ether, Mineral Oil, Talc, Hydrogenated Castor Oil, Fragrance (Parfum), Steareth-100, BHT.

Questions?

Call toll-free 1-800-450-7580